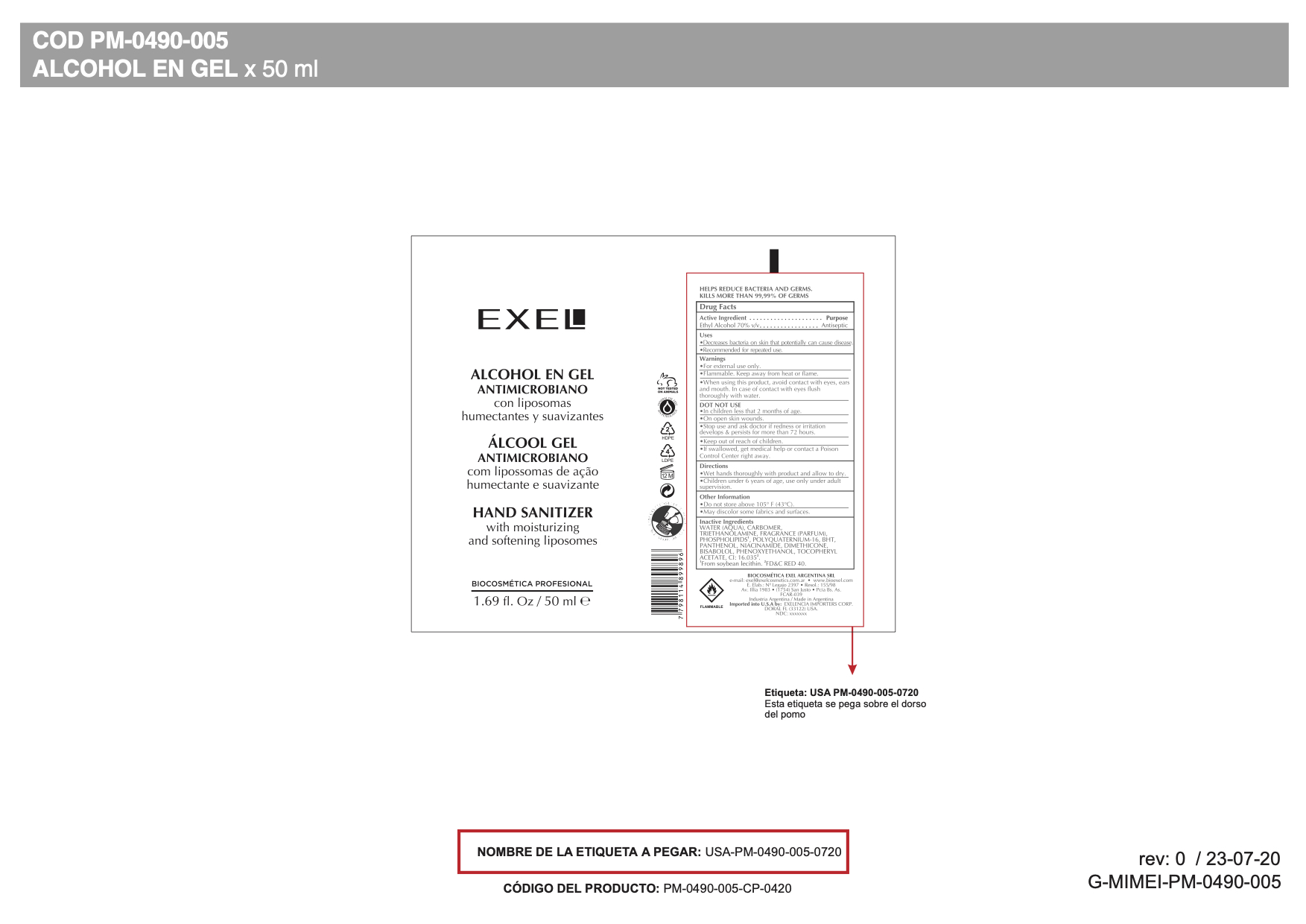 DRUG LABEL: Hand Sanitizer
NDC: 53863-002 | Form: GEL
Manufacturer: Exelencia Importers, Corp.
Category: otc | Type: HUMAN OTC DRUG LABEL
Date: 20240630

ACTIVE INGREDIENTS: ALCOHOL 70 mL/100 mL
INACTIVE INGREDIENTS: POLYQUATERNIUM-16 (N-VINYLPYRROLIDINONE:3-METHYL-1-VINYLIMIDAZOLIUM CHLORIDE (5:5)); BUTYLATED HYDROXYTOLUENE; PANTHENOL; EGG PHOSPHOLIPIDS; DIMETHICONE; PHENOXYETHANOL; .ALPHA.-TOCOPHEROL ACETATE; FD&C RED NO. 40; NIACINAMIDE; CARBOMER HOMOPOLYMER, UNSPECIFIED TYPE; TROLAMINE; WATER; LEVOMENOL

HAND SANITIZER

Active Ingredient

Ethyl Alcohol 70% v/v. Purpose: Antiseptic

Purpose

Antiseptic, Hand Sanitizer

Uses

Decreases bacteria on skin that pontetially can cause disease

Recommended for repeated use.

Warnings

For external use only.

Flammable. Keep away from heat or flame

When using this product, avoid contact with eyes, ears and mouth. In case of contact with eyes flush thoroughly with water.

Do not use

- In children less than 2 months of age.
- On open skin wounds.

When using this product, avoid contact with eyes, ears, and mouth. In case of contact with eyes flush thoroughly with water.
Stop use and ask a doctor if redness or irritation develops & persists for more than 72 hours.
Keep out of reach of children. If swallowed, get medical help or contact a Poison Control Center right away.

Stop use and ask a doctor if redness or irritation develops & persits for more than 72 hours.

Keep out of reach of children. If swallowed, get medical help or contact a Poison Control Center right away.

Directions

- Wet hands thoroughly with product and allow to dry.
- Children under 6 years of age, use only under adult supervision.

Inactive ingredients

Water (Aqua), Carbomer, Triethanolamine, Fragrance (Parfum), Phospholipids, Polyquaternium-16, BHT, Panthenol, Niacinamide, Dimethicone, Bisabolol, Phenoxyethanol, Tocopheryl Acetate, CI 16035

Fromsoybean lecithin. FD&C RED 40.

Other Information

Do not store above 105F (43C).

May discolor some fabrics and surfaces.

PACKAGE LABEL

EXEL

ALCOHOL EN GEL ANTIMICROBIANO

con liposomas humectantes y suavizantes

ALCOOL GEL ANTIMICROBIANO

com lipossomas de acao humectante e suavizante

HAND SANITIZER

with moisturizing and softening liposomes

BIOCOSMETICA PROFESIONAL

1.69 fl. Oz/50 ml e